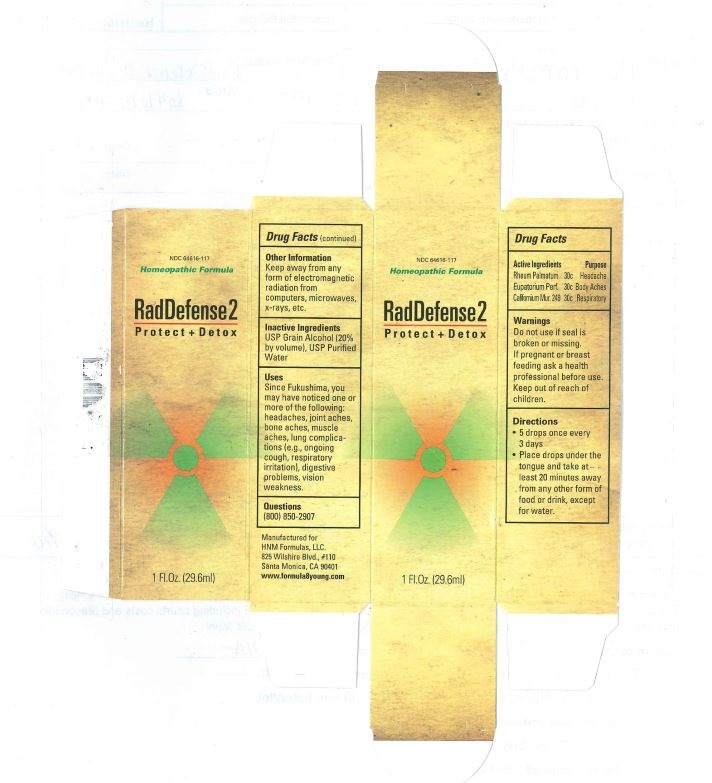 DRUG LABEL: RadDefense 2
NDC: 64616-117 | Form: LIQUID
Manufacturer: Vitality Works, Inc.
Category: homeopathic | Type: HUMAN OTC DRUG LABEL
Date: 20251217

ACTIVE INGREDIENTS: RHEUM PALMATUM ROOT 30 [hp_C]/0.03 mL; CALIFORNIUM CF-249 30 [hp_C]/0.03 mL; EUPATORIUM PERFOLIATUM FLOWERING TOP 30 [hp_C]/0.03 mL
INACTIVE INGREDIENTS: ALCOHOL; WATER

RadDefense2

Active Ingredients

Rheum palmatum 30C

Eupatorium Perfoliatum 30C

Californium muriaticum249 30C

Inactive Ingredients

USP Grain Alcohol (20% by volume), USP Purified water

Warnings

Do not use if seal is borken or missing.

If pregnant or breastfeeding, ask a health care professional before use.

Keep out of reach of children.

Other Information

Keep away from any form of electromagnetic radiation from computers, microwaves, x-rays, etc.

Distributed by

Distributed by HNM Formulas, LLC

825 Wilshire Blvd, #110

Santa Monica, CA 90401

www.formula8young.com

Uses

Since Fukushima, you may have noticed one or more of the following: headaches, joint aches, bone aches, muscle aches, lung complications (e.g. ongoing cough, respiratory irritation). digestive problems, vision weakness.

Warnings

Keep out of reach of children

Directions

5 drops every 3 days

Place drops under the tongue and take at least 20 minutes away from other food and drink, except water.

Uses

Since Fukushima, you may have noticed one or more of the following: headaches, joint aches, bone aches, muscle aches, lung complications, (e.g. ongoing cough, respiratory irritation), digestive problems, vision weakness.